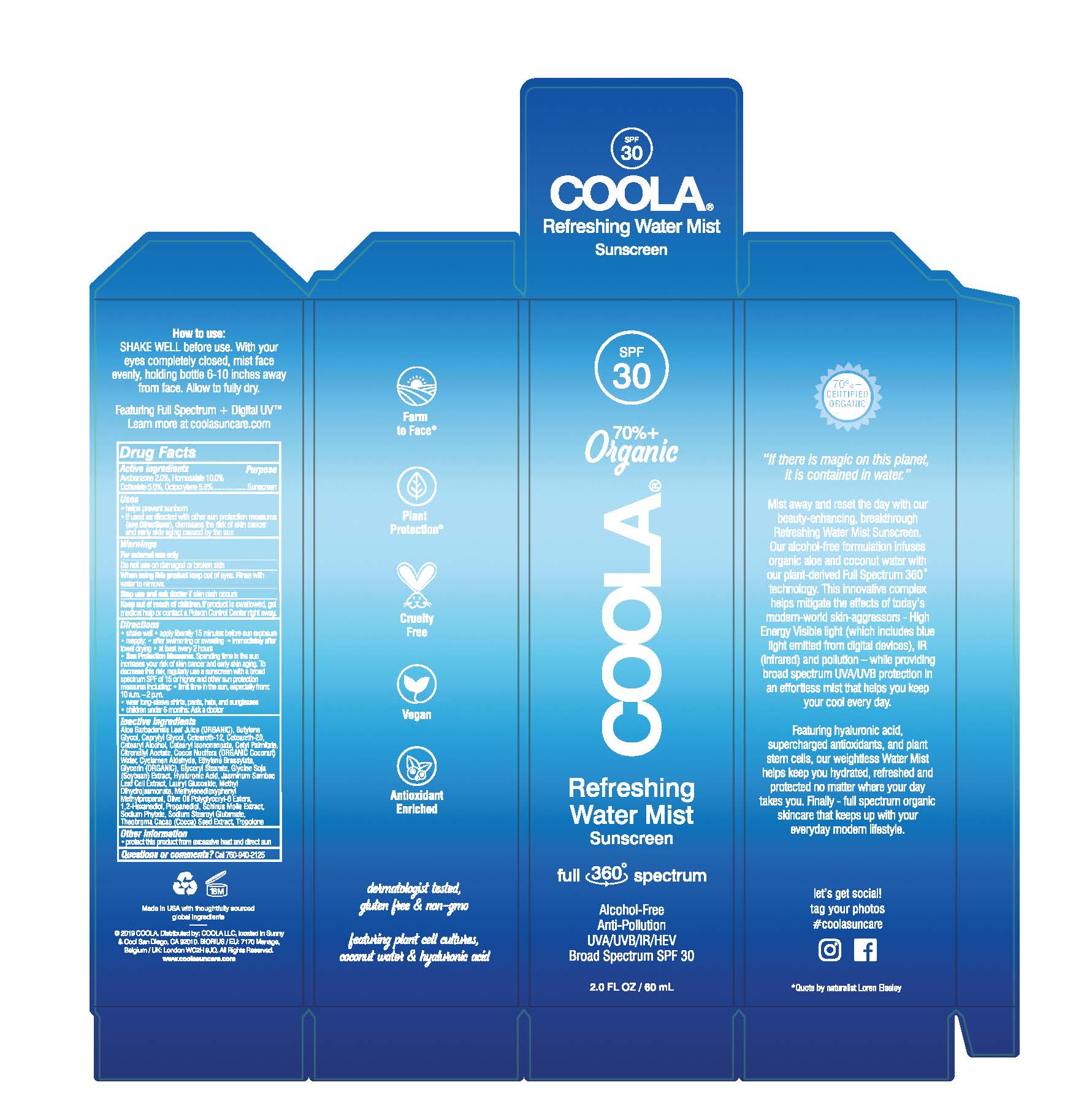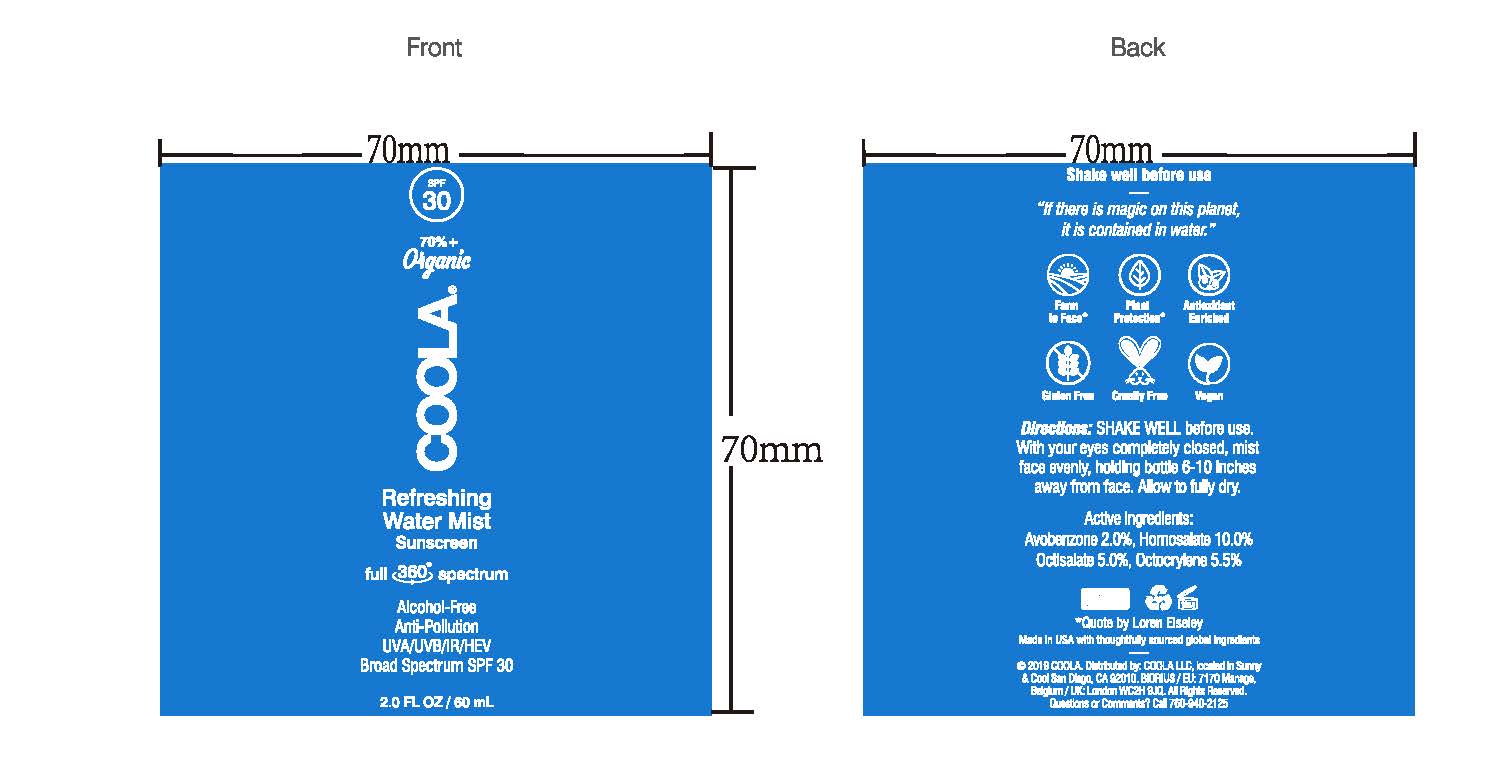 DRUG LABEL: COOLA Refreshing Water Mist Sunscreen
NDC: 21839-570 | Form: LIQUID
Manufacturer: GORDON LABORATORIES,INC
Category: otc | Type: HUMAN OTC DRUG LABEL
Date: 20191216

ACTIVE INGREDIENTS: AVOBENZONE 20 mg/1 mL; OCTISALATE 50 mg/1 mL; HOMOSALATE 100 mg/1 mL; OCTOCRYLENE 55 mg/1 mL
INACTIVE INGREDIENTS: WATER; JASMINUM SAMBAC FLOWER; SOYBEAN; GLYCERYL STEARATE SE; CETEARETH-12; BENZOIC ACID; ALCOHOL; ALOE VERA LEAF; PHYTATE SODIUM; GLYCERIN; MEDIUM-CHAIN TRIGLYCERIDES; 1,2-HEXANEDIOL; TROPOLONE; HYALURONATE SODIUM; BUTYLENE GLYCOL; CAPRYLYL GLYCOL; COCOA; SODIUM STEAROYL GLUTAMATE; SCHINUS MOLLE FRUITING TOP; ETHYL OLIVATE; COCONUT WATER; CETOSTEARYL ALCOHOL; PROPANEDIOL; LAURYL GLUCOSIDE; CETEARYL ISONONANOATE; CETYL PALMITATE; POLYOXYL 20 CETOSTEARYL ETHER

COOLA Refreshing Water Mist Sunscreen SPF 30

Active ingredients

Avobenzone 2.0%, Homosalate 10.0%, Octisalate 5.0%, Octocrylene 5.5%

Purpose

Sunscreen

Uses

* helps prevent sunburn

* if used as directed with other sun protection measures (see Directions), decreases the rise of skin cancer and early skin aging caused by the sun

Warnings

For external use only

Do not use on damaged or broken skin

When using this product keep out of eyes. Rinse with water to remove.

Stop use and ask doctor if skin rash occurs

Keep out of reach of children. If prodcut is swallowed, get medical help or contact Poison Control Center right away.

Do not use on damaged or broken skin

When using this product keep out of eyes. Rinse with water to remove

Stop use and ask doctor if skin rash occurs

Keep out of reach of children. If product is swallowed, get medical help or contact a Poison Control Center right away.

Directions

* shake well * apply liberally 15 minutes before sun exposure

* reapply: * after swimming or sweating * immediately after towel drying * at least every 2 hours

* Sun Protection Measures. Spending time in the sun increases your risk of skin cancer and early aging. To decrease this rise, regularly use a sunscreen with a broad spectrum SPF of 15 or higher and other sun protection measures including: * limit time in the sun, especially from: 10 a.m. – 2 p.m.

* wear long-sleve shirts, pants, hats, and sunglasses

* children under 6 months: Ask a doctor

Inactive ingredients

Aloe Barbadensis Leaf Juice (ORGANIC), Butylene Glycol, Caprylyl Glycol, Ceteareth-12, Ceteareth-20, Cetearyl Alcohol, Cetearyl Isononanoate, Cetyl Palmitate, Citronellyl Acetate, Cocos Nucifera (ORGANIC Coconut) Water, Cyclamen Aldehyde, Ethylene Brassylate, Glycerin (ORGANIC), Glyceryl Stearate, Glycine Soja (Soybean) Extract, Hyaluronic Acid, Jasminum Sambac Leaf Cell Extract, Lauryl Glucoside, Methyl Dihydrojasmonate, Methylenedioxyphenyl Methylpropanal, Olive Oil Polyglyceryl-6 Esters, 1,2-Hexanediol, Propanediol, Schinus Molle Extract, Sodium Phytate, Sodium Stearoyl Glutamate, Theobroma Cacao (Cocoa) Seed Extract, Tropolone

Other information

* protect this product from excessive heat and direct sun

Questions or comments? Call 760-940-2125